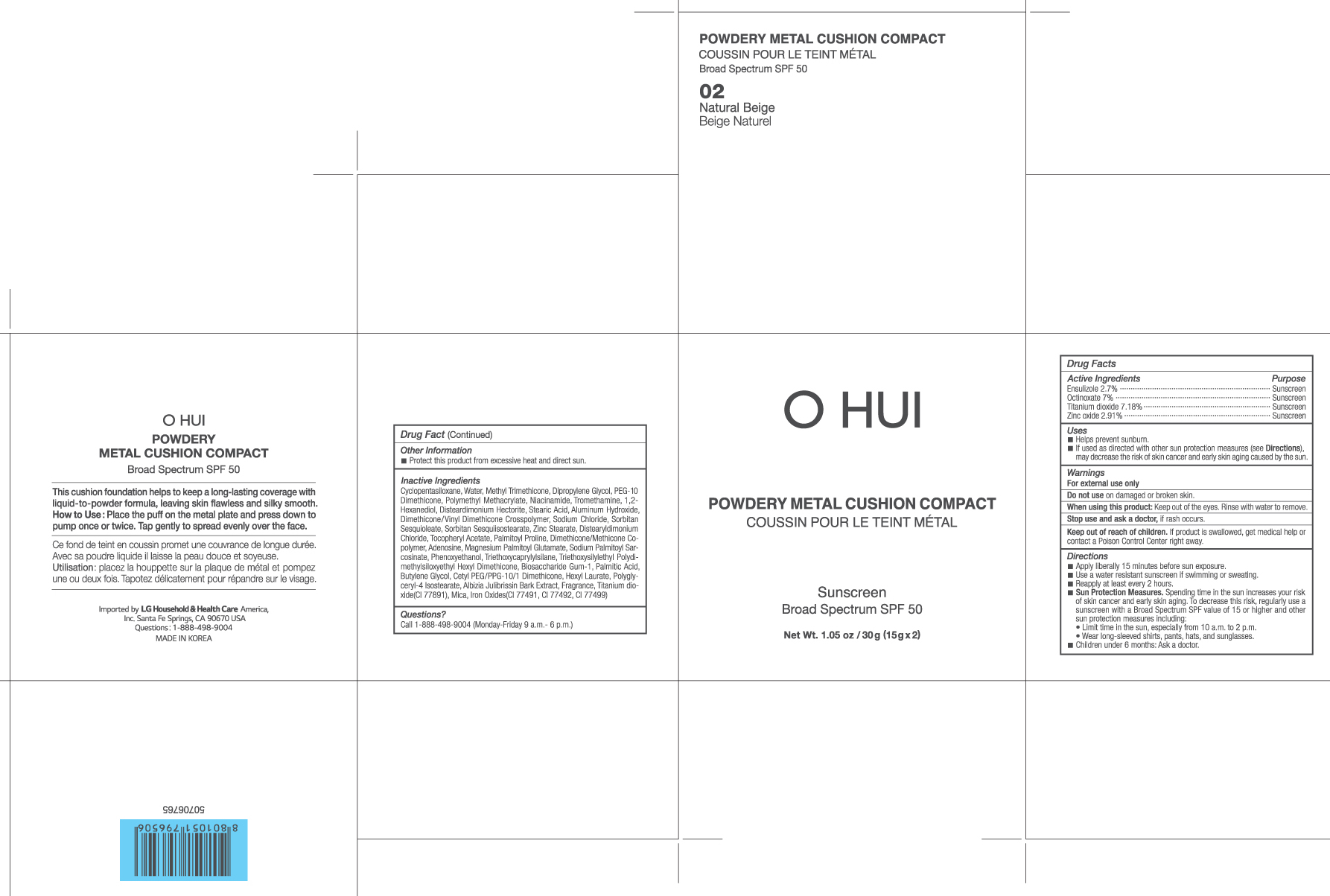 DRUG LABEL: OHUI Powdery Metal Cushion Compact 02 Natural Beige
NDC: 53208-603 | Form: POWDER
Manufacturer: LG Household and Health Care Inc
Category: otc | Type: HUMAN OTC DRUG LABEL
Date: 20160216

ACTIVE INGREDIENTS: TITANIUM DIOXIDE 1.077 g/15 g; ENSULIZOLE 0.405 g/15 g; OCTINOXATE 1.05 g/15 g; ZINC OXIDE 0.436 g/15 g
INACTIVE INGREDIENTS: DIPROPYLENE GLYCOL; MAGNESIUM PALMITOYL GLUTAMATE; PHENOXYETHANOL; ALUMINUM HYDROXIDE; WATER; ADENOSINE; SODIUM PALMITOYL SARCOSINATE; TRIETHOXYCAPRYLYLSILANE; PALMITIC ACID; HEXYL LAURATE; POLYGLYCERYL-4 ISOSTEARATE; ALBIZIA JULIBRISSIN BARK; NIACINAMIDE; BIOSACCHARIDE GUM-1; BUTYLENE GLYCOL; CETYL PEG/PPG-10/1 DIMETHICONE (HLB 2); MICA; PEG-10 DIMETHICONE (600 CST); POLY(METHYL METHACRYLATE; 450000 MW); TROMETHAMINE; 1,2-HEXANEDIOL; PALMITOYL PROLINE; CYCLOMETHICONE 5; METHYL TRIMETHICONE; DISTEARDIMONIUM HECTORITE; STEARIC ACID; SORBITAN SESQUIOLEATE; ZINC STEARATE; DISTEARYLDIMONIUM CHLORIDE; ALPHA-TOCOPHEROL ACETATE; DIMETHICONE/VINYL DIMETHICONE CROSSPOLYMER (SOFT PARTICLE); SODIUM CHLORIDE

ACTIVE INGREDIENTS

ENSULIZOLE 2.7%, OCTINOXATE 7%, TITANIUM DIOXIDE 7.18%, ZINC OXIDE 2.91%

PURPOSE

Sunscreen

USES

- Helps prevent sunburn.
- If used as directed with other sun protection measures (see Directions),

decreases the risk of skin cancer and early skin aging caused by the sun.

WARNINGS

For external use only

Do not use on damaged or broken skin.

When using this product: Kepp out of the eyes. Rinse with water to remove.

Stop use and ask doctor, if rash occurs.

Keep out of reach of children. If product is swallowed, get medical help or

contact a Posion Control Center right away.

DIRECTIONS

- Apply liberally 15 minutes before sun exposure.
- Use a water resistant sunscreen if swimming or sweating.
- Reapply at least every 2 hours.
- Sun Protection Measures. Spending time in the sun increases your risk

Of skin cancer and early skin aging. To decrease this risk, regularly use a

Sunscreen with a Broad Spectrum SPF value of 15 or higher and other

sun protection measures including:

- Limit time in the sun, especially from 10 a.m. to 2 p.m.

- Wear longsleeved shirts, pants, hats, and sunglasses.

- Children under 6 months: Ask a doctor.

OTHER INFORMATION

- Protect this product from excessive heat and direct sun.

INACTIVE INGREDIENTS

CYCLOPENTASILOXANE, WATER, METHYL TRIMETHICONE, DIPROPYLENE GLYCOL, PEG-10 DIMETHICONE, POLYMETHYL METHACRYLATE, NIACINAMIDE, TROMETHAMINE, 1,2-HEXANEDIOL, DISTEARDIMONIUM HECTORITE, STEARIC ACID, ALUMINUM HYDROXIDE, DIMETHICONE/VINYL DIMETHICONE CROSSPOLYMER, SODIUM CHLORIDE, SORBITAN SESQUIOLEATE, SORBITAN SESQUIISOSTEARATE, ZINC STEARATE, DISTEARYLDIMONIUM CHLORIDE, TOCOPHERYL ACETATE, PALMITOYL PROLINE, DIMETHICONE/METHICONE COPOLYMER, ADENOSINE, MAGNESIUM PALMITOYL GLUTAMATE, SODIUM PALMITOYL SARCOSINATE, PHENOXYETHANOL, TRIETHOXYCAPRYLYLSILANE, TRIETHOXYSILYLETHYL POLYDIMETHYLSILOXYETHYL HEXYL DIMETHICONE, BIOSACCHARIDE GUM-1, PALMITIC ACID, BUTYLENE GLYCOL, CETYL PEG/PPG-10/1 DIMETHICONE, HEXYL LAURATE, POLYGLYCERYL-4 ISOSTEARATE, ALBIZIA JULIBRISSIN BARK EXTRACT, FRAGRANCE, TITANIUM DIOXIDE(CI 77891), MICA, IRON OXIDES(CI 77492), IRON OXIDES(CI 77491), IRON OXIDES(CI 77499)

PRINCIPAL DISPLAY PANEL

OHUI Powdery Metal Cushion Compact

Sunscreen Broad Spectrum SPF 50

02 Natural Beige

Net Wt. 1.05 oz / 30 g (15gx2)